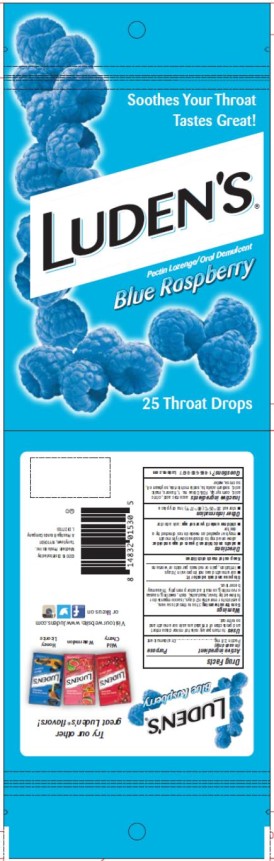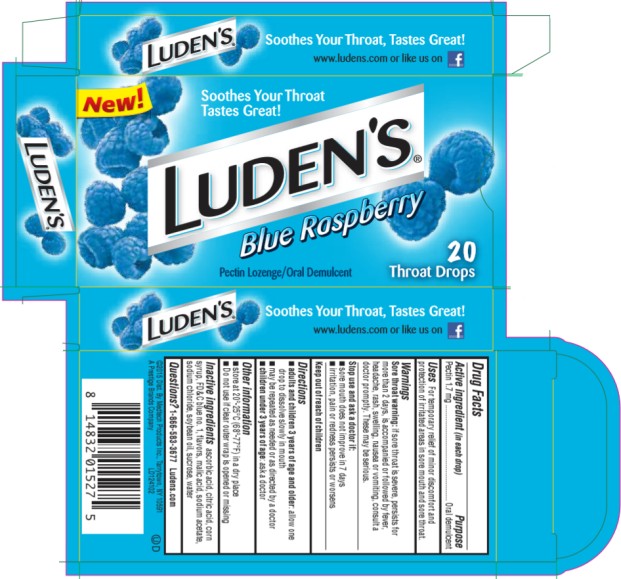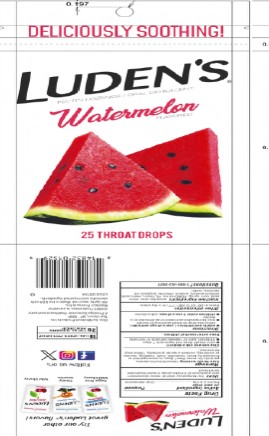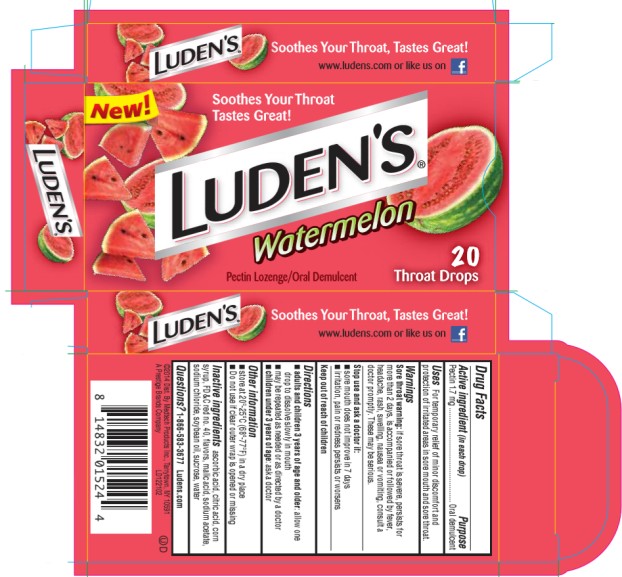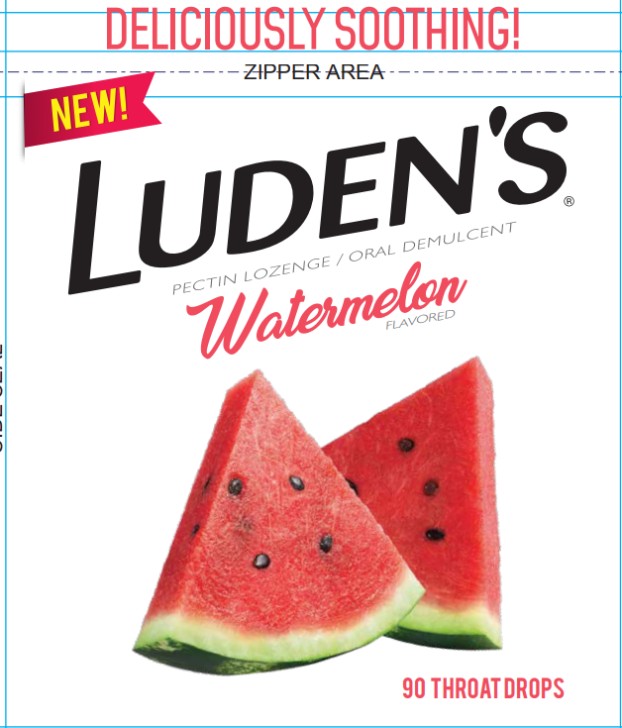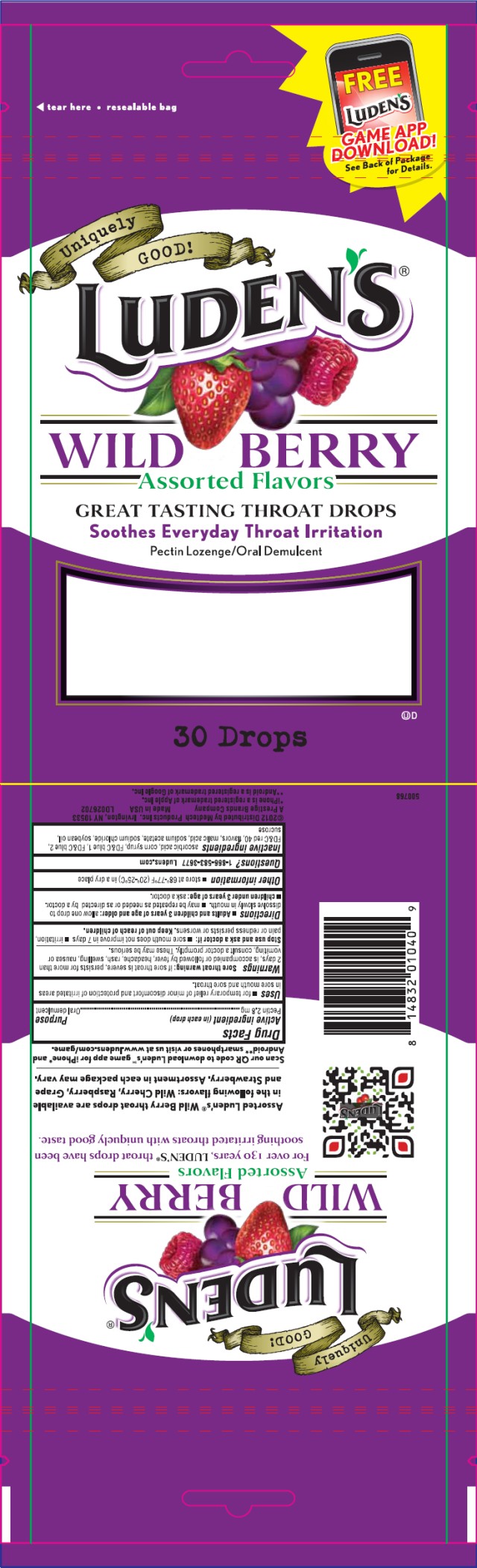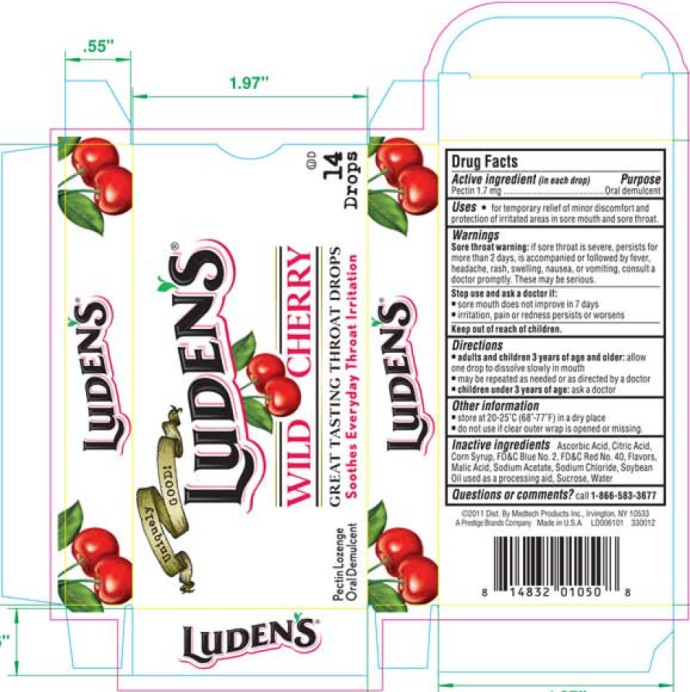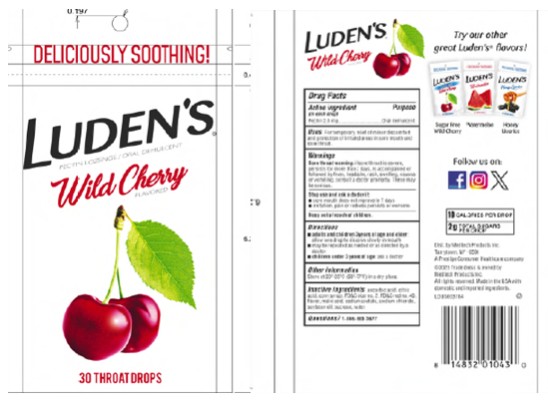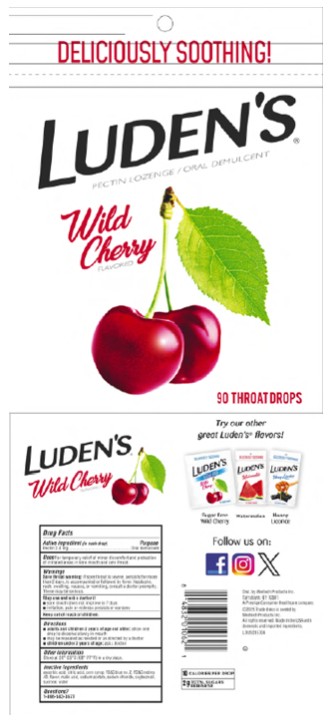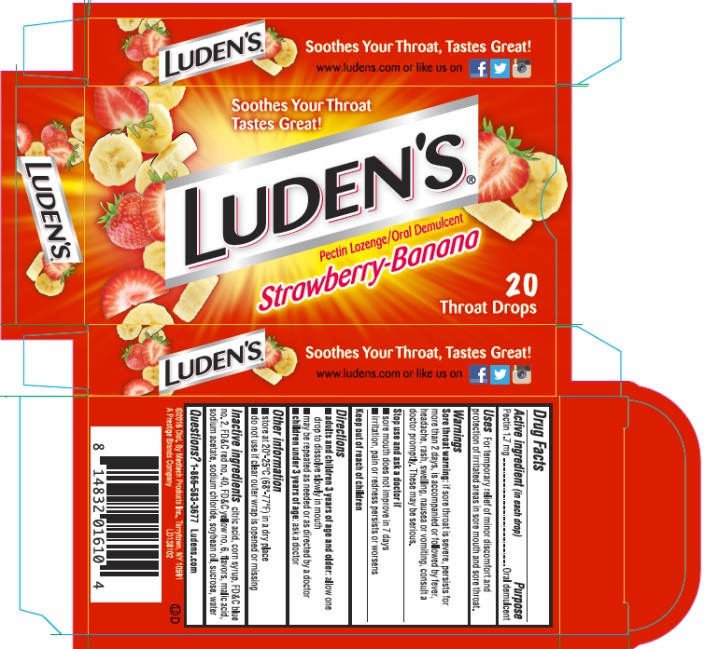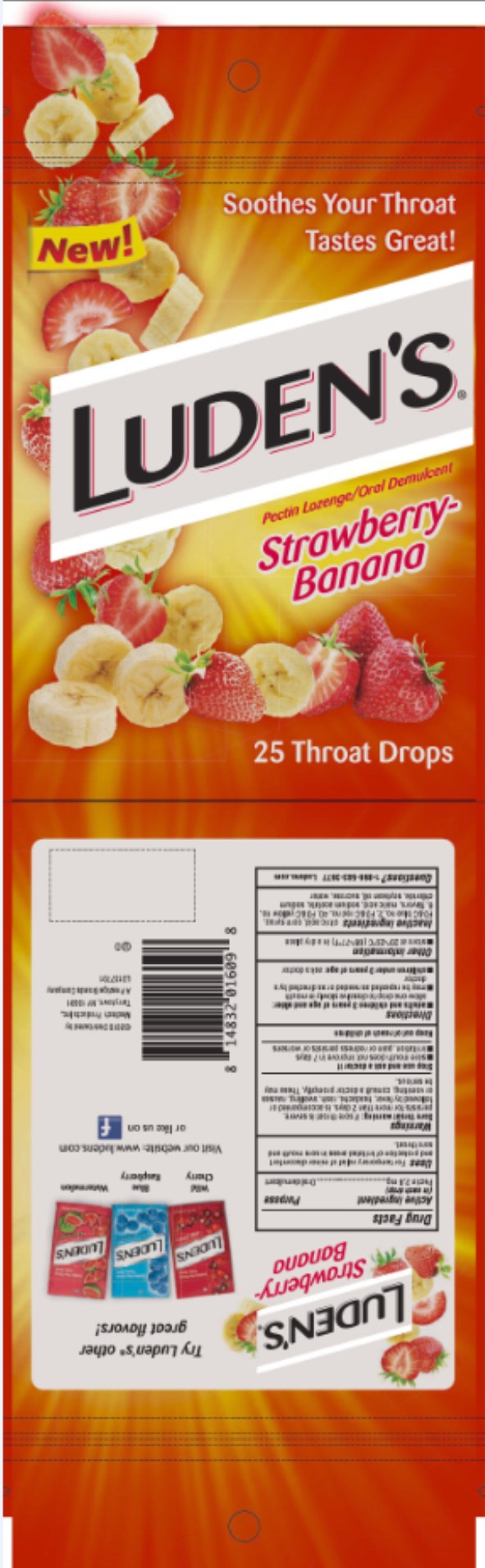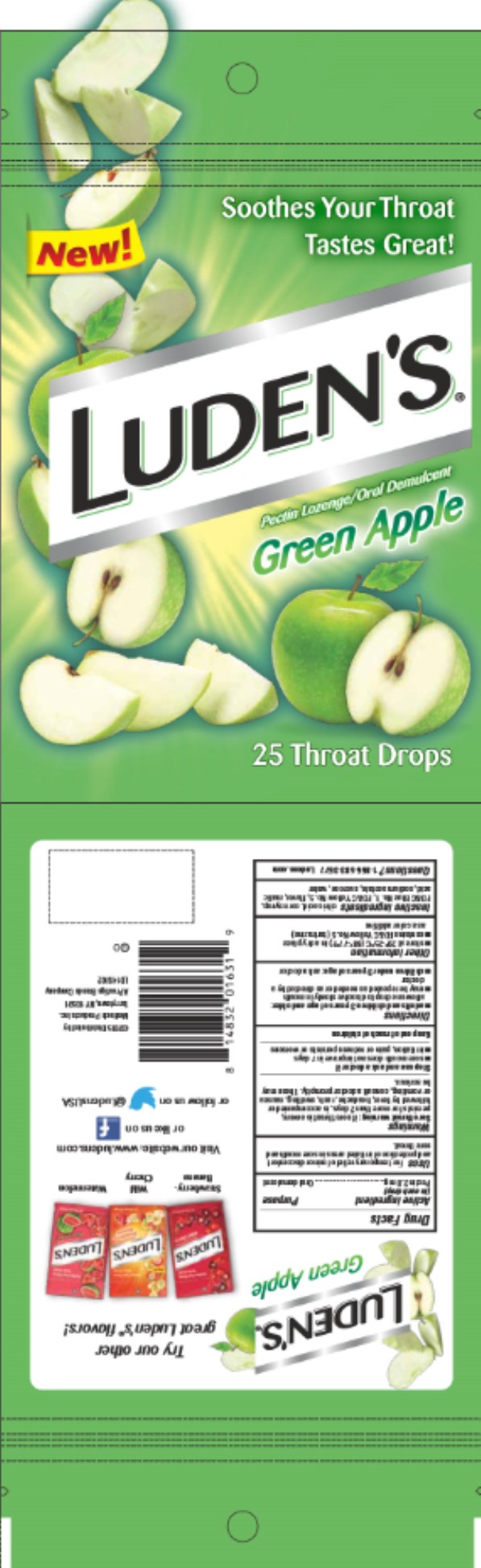 DRUG LABEL: Ludens Berry Assortment Throat Drops
NDC: 52183-289 | Form: LOZENGE
Manufacturer: Prestige Brands Holdings, Inc.
Category: otc | Type: HUMAN OTC DRUG LABEL
Date: 20251205

ACTIVE INGREDIENTS: PECTIN 2.8 mg/1 1
INACTIVE INGREDIENTS: ASCORBIC ACID; CITRIC ACID MONOHYDRATE; CORN SYRUP; FD&C BLUE NO. 2; FD&C RED NO. 40; MALIC ACID; SODIUM ACETATE; SODIUM CHLORIDE; SOYBEAN OIL; SUCROSE; FD&C BLUE NO. 1

Ludens Pectin Throat Lozenges

Luden’s Blue Raspberry Throat Drops

Drug Facts

Active ingredient (in each drop)

Pectin 2.8 mg

Purpose

Oral demulcent

Uses

For temporary relief of minor discomfort and protection of irritated areas in sore mouth and sore throat.

Warnings

Sore throat warning: if sore throat is severe, persists for more than 2 days, is accompanied or followed by fever, headache, rash, swelling, nausea or vomiting, consult a doctor promptly. These may be serious.

Stop use and ask a doctor if

- sore mouth does not improve in 7 days
- irritation, pain or redness persists or worsens.

Directions

- Adults and children 3 years of age and older: allow one drop to dissolve slowly in mouth.
- may be repeated as needed or as directed by a doctor.
- children under 3 years of age: ask a doctor

Other information

- store at 20º-25ºC (68º-77ºF) in a dry place

Questions?

1-866-583-3677 Ludens.com

Inactive ingredients

ascorbic acid, citric acid, corn syrup, FD&C blue no. 1, flavors, malic acid, sodium acetate, sodium chloride, soybean oil, sucrose, water

Luden’s Blue Raspberry Throat Drops

Drug Facts

Active ingredient (in each drop)

Pectin 1.7 mg

Purpose

Oral demulcent

Uses

For temporary relief of minor discomfort and protection of irritated areas in sore mouth and sore throat.

Warnings

Sore throat warning: if sore throat is severe, persists for more than 2 days, is accompanied or followed by fever, headache, rash, swelling, nausea or vomiting, consult a doctor promptly. These may be serious.

Stop use and ask a doctor if

- sore mouth does not improve in 7 days
- irritation, pain or redness persists or worsens.

Directions

- Adults and children 3 years of age and older: allow one drop to dissolve slowly in mouth.
- may be repeated as needed or as directed by a doctor.
- children under 3 years of age: ask a doctor

Other information

- store at 20º-25ºC (68º-77ºF) in a dry place

Questions?

1-866-583-3677 Ludens.com

Inactive ingredients

ascorbic acid, citric acid, corn syrup, FD&C blue no. 1, flavors, malic acid, sodium acetate, sodium chloride, soybean oil, sucrose, water

Luden’s Watermelon Throat Drops

Drug Facts

Active ingredient (in each drop)

Pectin 2.8 mg

Purpose

Oral demulcent

Uses

For temporary relief of minor discomfort and protection of irritated areas in sore mouth and sore throat.

Warnings

Sore throat warning: if sore throat is severe, persists for more than 2 days, is accompanied or followed by fever, headache, rash, swelling, nausea or vomiting, consult a doctor promptly. These may be serious.

Stop use and ask a doctor if:

- sore mouth does not improve in 7 days
- irritation, pain or redness persists or worsens

Directions

- adults and children 3 years of age and older: allow one drop to dissolve slowly in mouth
- may be repeated as needed or as directed by a doctor
- children under 3 years of age: ask a doctor

Other information

- store at 20º-25ºC (68º-77ºF) in a dry place

Inactive ingredients

ascorbic acid, citric acid, corn syrup, FD&C red no. 40, flavor, malic acid, sodium acetate, sodium chloride, soybean oil, sucrose, water

Questions?

1-866-583-3677

Luden’s Watermelon Throat Drops

Drug Facts

Active ingredient (in each drop)

Pectin 1.7 mg

Purpose

Oral demulcent

Uses

For temporary relief of minor discomfort and protection of irritated areas in sore mouth and sore throat.

Warnings

Sore throat warning: if sore throat is severe, persists for more than 2 days, is accompanied or followed by fever, headache, rash, swelling, nausea or vomiting, consult a doctor promptly. These may be serious.

Stop use and ask a doctor if

- sore mouth does not improve in 7 days
- irritation, pain or redness persists or worsens.

Directions

- Adults and children 3 years of age and older: allow one drop to dissolve slowly in mouth.
- may be repeated as needed or as directed by a doctor.
- children under 3 years of age: ask a doctor

Other information

- store at 20º-25ºC (68º-77ºF) in a dry place

Questions?

1-866-583-3677 Ludens.com

Inactive ingredients

ascorbic acid, citric acid, corn syrup, FD&C red no. 40, flavors, malic acid, sodium acetate, sodium chloride, soybean oil, sucrose, water

Luden’s Wild Berry Throat Drops

Drug Facts

Active ingredient (in each drop)

Pectin 2.8 mg

Purpose

Oral demulcent

Uses

- for temporary relief of minor discomfort and protection of irritated areas in sore mouth and sore throat.

Warnings

Sore throat warning: if sore throat is severe, persists for more than 2 days, is accompanied or followed by fever, headache, rash, swelling, nausea or vomiting, consult a doctor promptly. These may be serious.

Stop use and ask a doctor if

- sore mouth does not improve in 7 days
- irritation, pain or redness persists or worsens.

Directions

- Adults and children 3 years of age and older: allow one drop to dissolve slowly in mouth.
- may be repeated as needed or as directed by a doctor.
- children under 3 years of age: ask a doctor

Other information

- store at 68º-77ºF (20º-25ºC) in a dry place

Questions?

1-866-583-3677 Ludens.com

Inactive ingredients

ascorbic acid, citric acid, corn syrup, FD&C blue 1, FD&C blue 2, FD&C red 40, flavors, malic acid, sodium acetate, sodium chloride, soybean oil, and sucrose.

Luden’s Wild Cherry Throat Drops

Drug Facts

Active ingredient (in each drop)

Pectin 1.7 mg

Purpose

Oral demulcent

Uses

- for temporary relief of minor discomfort and protection of irritated areas in sore mouth and sore throat.

Warnings

Sore throat warning: if sore throat is severe, persists for more than 2 days, is accompanied or followed by fever, headache, rash, swelling, nausea or vomiting, consult a doctor promptly. These may be serious.

Stop use and ask a doctor if

- sore mouth does not improve in 7 days
- irritation, pain or redness persists or worsens

Directions

- adults and children 3 years of age and older: allow one drop to dissolve slowly in mouth.
- may be repeated as needed or as directed by a doctor
- children under 3 years of age: ask a doctor

Other information

- store at 20-25ºC (68º-77ºF) in a dry place
- do not use if clear outer wrap is opened or missing.

Inactive ingredients

Ascorbic Acid, Citric Acid, Corn Syrup, FD&C Blue No. 2, FD&C Red No. 40, Flavors, Malic Acid, Sodium Acetate, Sodium Chloride, Soybean Oil used as a processing aid, Sucrose, Water

Questions or comments?

call 1-866-583-3677

Luden’s Wild Cherry Throat Drops

Drug Facts

Active ingredient (in each drop)

Pectin 2.8 mg

Purpose

Oral demulcent

Uses

- for temporary relief of minor discomfort and protection of irritated areas in sore mouth and sore throat

Warnings

Sore throat warning: if sore throat is severe, persists for more than 2 days, is accompanied or followed by fever, headache, rash, swelling, nausea or vomiting, consult a doctor promptly. These may be serious.

Stop use and ask a doctor if

- sore mouth does not improve in 7 days
- irritation, pain or redness persists or worsens

Directions

- adults and children 3 years of age and older: allow one drop to dissolve slowly in mouth.
- may be repeated as needed or as directed by a doctor.
- children under 3 years of age: ask a doctor

Other information

- store at 20-25ºC (68-77ºF) in a dry place

Inactive ingredients

ascorbic acid, citric acid, corn syrup, FD&C blue no. 2, FD&C red no. 40, flavors, malic acid, sodium acetate, sodium chloride, soybean oil (processing aid), sucrose, water

Questions or comments?

call 1-866-583-3677

Luden's Strawberry Banana Throat Drops

Drug Facts

Active ingredient (in each drop)

Pectin 1.7 mg

Purpose

Oral demulcent

Uses

For temporary relief of minor discomfort and protection of irritated areas in sore mouth and sore throat.

Warnings

Sore throat warning: if sore throat is severe, persists for more than 2 days, is accompanied or followed by fever, headache, rash, swelling, nausea or vomiting, consult a doctor promptly. These may be serious.

Stop use and ask a doctor if

• sore mouth does not improve in 7 days

• irritation, pain or redness persists or worsens

Directions

• adults and children 3 years of age and older: allow one drop to dissolve slowly in mouth

• may be repeated as needed or as directed by a doctor

• children under 3 years of age: ask a doctor

Other information

• store at 20º-25ºC (68º-77ºF) in a dry place

• do not use if clear outer wrap is opened or missing

Inactive ingredients

citric acid, corn syrup, FD&C blue no. 2, FD&C red no. 40, FD&C yellow no. 6, flavors, malic acid, sodium acetate, sodium chloride, soybean oil, sucrose, water

Questions?

1-866-583-3677 Ludens.com

Luden's Strawberry Banana Throat Drops

Drug Facts

Active ingredient (in each drop)

Pectin 2.8 mg

Purpose

Oral demulcent

Uses

For temporary relief of minor discomfort and protection of irritated areas in sore mouth and sore throat.

Warnings

Sore throat warning: if sore throat is severe, persists for more than 2 days, is accompanied or followed by fever, headache, rash, swelling, nausea or vomiting, consult a doctor promptly. These may be serious.

Stop use and ask a doctor if

• sore mouth does not improve in 7 days

• irritation, pain or redness persists or worsens

Directions

• adults and children 3 years of age and older: allow one drop to dissolve slowly in mouth

• may be repeated as needed or as directed by a doctor

• children under 3 years of age: ask a doctor

Other information

• store at 20º-25ºC (68º-77ºF) in a dry place

• do not use if clear outer wrap is opened or missing

Inactive ingredients

citric acid, corn syrup, FD&C blue no. 2, FD&C red no. 40, FD&C yellow no. 6, flavors, malic acid, sodium acetate, sodium chloride, soybean oil, sucrose, water

Questions?

1-866-583-3677 Ludens.com

Luden's Green Apple Throat Drops

Drug Facts

Active ingredient (in each drop)

Pectin 2.8 mg

Purpose

Oral demulcent

Uses

For temporary relief of minor discomfort and protection of irritated areas in sore mouth and sore throat.

Warnings

Sore throat warning: if sore throat is severe, persists for more than 2 days, is accompanied or followed by fever, headache, rash, swelling, nausea or vomiting, consult a doctor promptly. These may be serious.

Stop use and ask a doctor if

• sore mouth does not improve in 7 days

• irritation, pain or redness persists or worsens

Directions

• adults and children 3 years of age and older: allow one drop to dissolve slowly in mouth

• may be repeated as needed or as directed by a doctor

• children under 3 years of age: ask a doctor

Other information

• store at 20º-25ºC (68º-77ºF) in a dry place

• contains FD&C Yellow No. 5 (tartrazine)as a color additive

Inactive ingredients

citric acid, corn syrup, FD&C Blue No. 1, FD&C Yellow No. 5, flavor, malic acid, sodium acetate, sodium choride, sucrose, water

Questions?

1-866-583-3677 Ludens.com

Principal Display Panel

Luden’s
Pectin Lozenge/Oral Demulcent
Blue Raspberry
25 Throat Drops

Principal Display Panel

Luden’s
Pectin Lozenge/Oral Demulcent
Blue Raspberry
20 Throat Drops

Principal Display Panel

Luden’s
Pectin Lozenge/Oral Demulcent
Watermelon
25 Throat Drops

Principal Display Panel

Luden’s
Pectin Lozenge/Oral Demulcent
Watermelon
20 Throat Drops

Principal Display Panel

Luden’s
Pectin Lozenge/Oral Demulcent
Watermelon
90 Throat Drops

Principal Display Panel

Luden’s
Pectin Lozenge/Oral Demulcent
Wild Berry
30 Drops

Principal Display Panel

Luden’s
Pectin Lozenge
Oral Demulcent
Wild Cherry
14 Drops

Principal Display Panel

Luden’s
Pectin Lozenge/Oral Demulcent
Wild Cherry
30 Drops

Principal Display Panel

Luden’s
Pectin Lozenge/Oral Demulcent
Wild Cherry
90 Drops

Principal Display Panel

Luden’s Strawberry-Banana
Pectin lozenge / Oral Demulcent
20 Throat drops

Principal Display Panel

Luden’s Strawberry-Banana
Pectin lozenge / Oral Demulcent
25 Throat drops

Principal Display Panel

Luden’s Green Apple
Pectin lozenge / Oral Demulcent
25 Throat drops